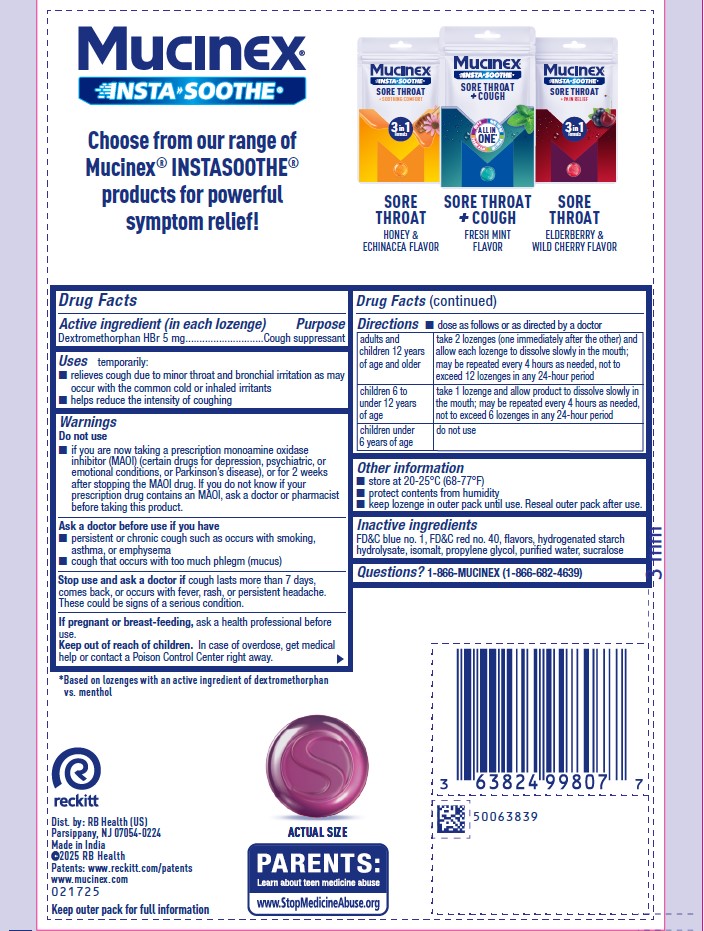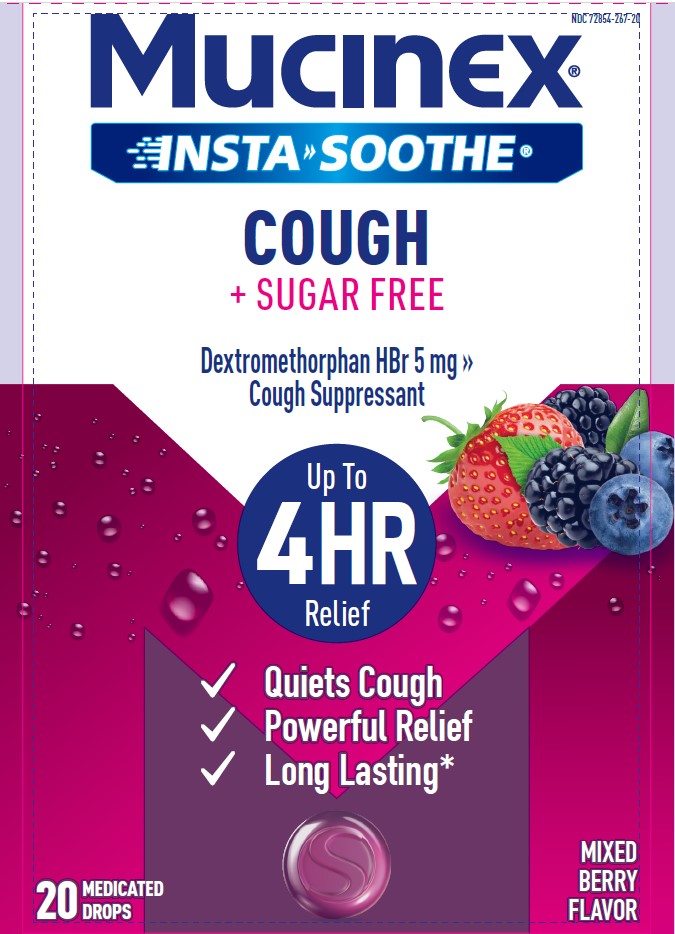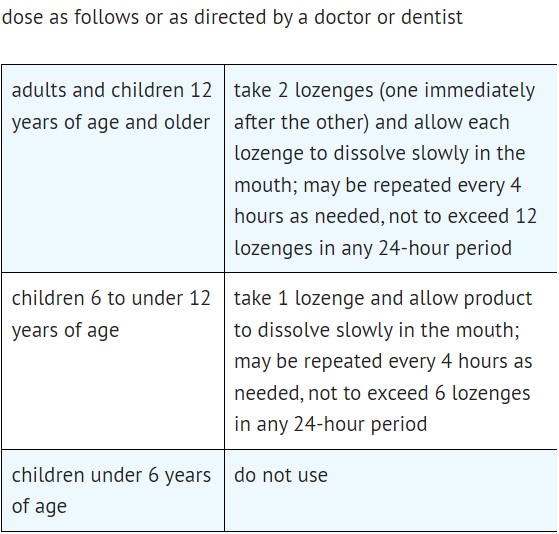 DRUG LABEL: MUCINEX INSTASOOTHE
NDC: 72854-267 | Form: LOZENGE
Manufacturer: RB Health (US) LLC
Category: otc | Type: HUMAN OTC DRUG LABEL
Date: 20241011

ACTIVE INGREDIENTS: DEXTROMETHORPHAN HYDROBROMIDE 5 mg/1 1
INACTIVE INGREDIENTS: FD&C RED NO. 40; ISOMALT; PROPYLENE GLYCOL; FD&C BLUE NO. 1; WATER; SUCRALOSE; HYDROGENATED STARCH HYDROLYSATE

MUCINEX® InstaSoothe™

Active Ingredient; (in each Lozenge) | Purpose
Dextromethorphan HBr 5 mg | Cough suppressant

PURPOSE

Dextromethorphan HBr 5 mg: Cough suppressant

Uses

Temporarily:
■ relieves cough due to minor throat and bronchial irritation as may occur with the common
cold or inhaled irritants
■ helps reduce the intensity of coughing

Warnings

Do Not Use
■ if you are now taking a prescription monoamine oxidase inhibitor (MAOI) (certain drugs for
depression, psychiatric, or emotional conditions, or Parkinson’s disease), or for 2 weeks after
stopping the MAOI drug. If you do not know if your prescription drug contains an MAOI, ask a
doctor or pharmacist before taking this product.

Ask a doctor before use if you have
■ persistent or chronic cough such as occurs with smoking, asthma, or emphysema
■ cough that occurs with too much phlegm (mucus)

Stop use and ask a doctor if cough lasts more than 7 days, comes back, or occurs with fever, rash, or persistent headache.

These could be signs of a serious condition.

If pregnant or breastfeeding, ask a health professional before use.

Keep out of reach of children. In case of overdose, get medical help or contact a Poison Control Center right away

Other Infomation

- store at 20-25°C (68-77°F)
- protect contents from humidity
- keep lozenge in outer pack until use. Reseal outer pack after use.

Inactives

FD&C blue no. 1, FD&C red no. 40, flavors, hydrogenated starch
hydrolysate, isomalt, propylene glycol, purified water, sucralose

Questions

1-866-MUCINEX (1-866-682-4639)

Dist. by: RB Health (US)
Parsippany, NJ 07054-0224
Made in India
2024 RB Health
Patents: www/reckitt.com/patents
www.mucinex.com

PACKAGE LABEL

NDC 72854-267-20

Mucinex®
INSTA>>SOOTHE® COUGH + SUGAR FREE

Dextromethorphan HBr 5 mg >> Cough Suppressant

Up to 4HR Relief

✔Quiets Cough
✔ Powerful Relief
✔ Long Lasting*”

20 MEDICATED DROPS - MIXED BERRY FLAVOR